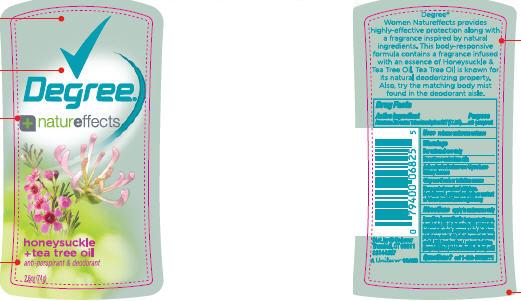 DRUG LABEL: Degree Nature Effects Honeysuckle and Tea Tree Oil
NDC: 64942-1118 | Form: STICK
Manufacturer: Conopco Inc. d/b/a Unilever
Category: otc | Type: HUMAN OTC DRUG LABEL
Date: 20100216

ACTIVE INGREDIENTS: Aluminum Zirconium Tetrachlorohydrex GLY 17.8 g/100 g

Degree Honeysuckle and Tea Tree Oil Antiperspirant and Deodorant back and front PACKAGE LABEL.PRINCIPAL DISPLAY PANEL and Drug Facts

Active ingredient Purpose

Aluminum Zirconium Tetrachlorohydrex GLY (17.8%)...................anti-perspirant

Warning
For external use only

Do not use on broken skin

Ask a doctor before use if you havekidney disease

Keep out of reach of children.

If swallowed, get medical help or contact a Poison Control Center right away

Stop use if rash or irritation occurs.

Keep out of reach of children.
If swallowed, get medical help or contact a Poison Control Center right away

INACTIVE INGREDIENT

Cyclopentasiloxane, Stearyl Alcohol, C12-15 Alkyl Benzoate, PPG-14 Butyl Ether, Hydrogenated Castor Oil, Fragrance (Parfum), Dimethicone, Polyethylene, Steareth-100, Helianthus Annuus (Sunflower) Seed Oil, BHT, Propylene Glycol, Lonicera Caprifolium (Honeysuckle) Extract, Melaleuca Alternifolia (Tea Tree) Leaf Oil.

Questions? call 1-866-DEGREE1

PACKAGE LABEL

PDP 2.6 oz